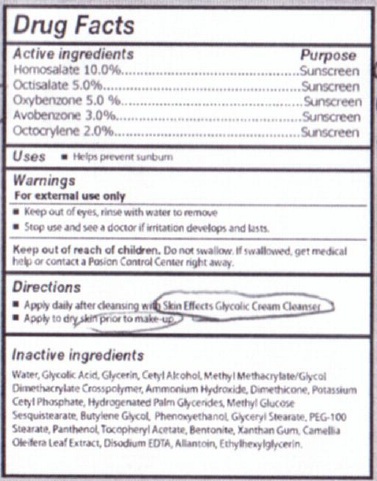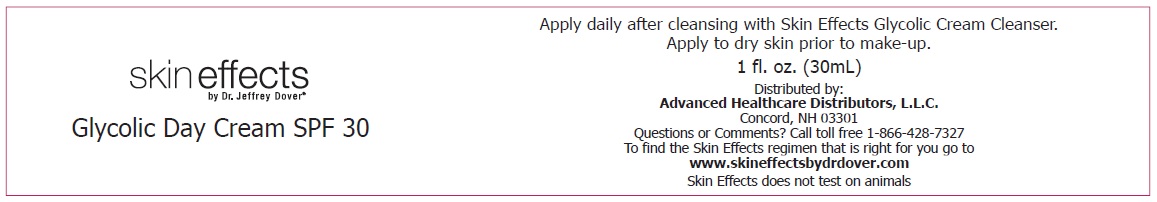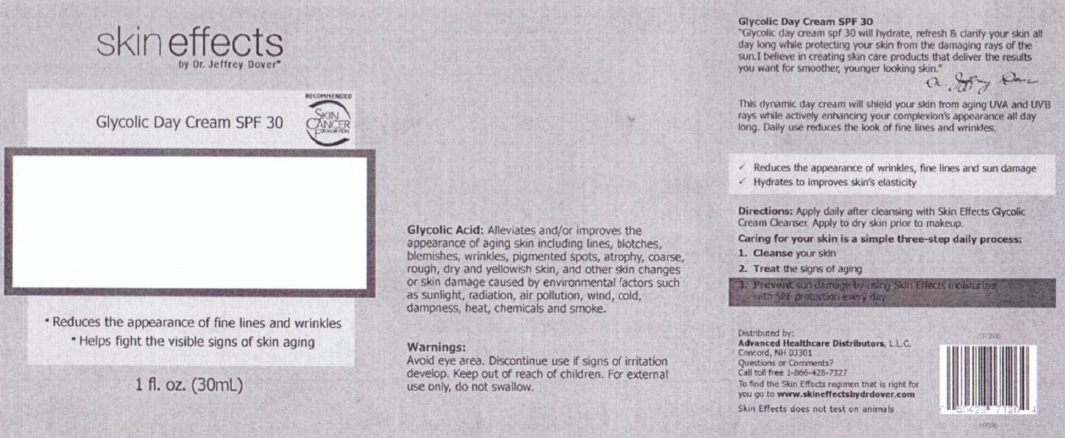 DRUG LABEL: Skin Effects by Dr. Jeffrey Dover Glycolic Day
NDC: 42877-092 | Form: CREAM
Manufacturer: Diversified Global Technologies DBA Diversified Distribution
Category: otc | Type: HUMAN OTC DRUG LABEL
Date: 20110504

ACTIVE INGREDIENTS: HOMOSALATE 10 mL/100 mL; OCTISALATE 5 mL/100 mL; OXYBENZONE 5 mL/100 mL; AVOBENZONE 3 mL/100 mL; OCTOCRYLENE 2 mL/100 mL
INACTIVE INGREDIENTS: WATER; GLYCOLIC ACID; GLYCERIN; CETYL ALCOHOL; METHYL METHACRYLATE; GLYCOL DIMETHACRYLATE; AMMONIA; DIMETHICONE; POTASSIUM CETYL PHOSPHATE; HYDROGENATED PALM GLYCERIDES; DEXTROSE; BUTYLENE GLYCOL; PHENOXYETHANOL; GLYCERYL MONOSTEARATE; POLYETHYLENE GLYCOL 4500; PEG-100 STEARATE; PANTHENOL; ACETATE ION; BENTONITE; XANTHAN GUM; CAMELLIA OLEIFERA LEAF; EDETATE DISODIUM; ALLANTOIN; ETHYLHEXYLGLYCERIN

SKIN EFFECTS BY DR. JEFFREY DOVER GLYCOLIC DAY CREAM SPF 30

Drug Facts

Active Ingredients Purpose

Homosalate 10.0%.......................................Sunscreen

Octisalate 5.0%........................................Sunscreen

Oxybenzone 5.0%..........................................Sunscreen

Avobenzone 3.0%........................................Sunscreen

Octocrylene 2.0%...........................................Sunscreen

PURPOSE

Uses: helps prevent sunburn.

WARNINGS:
For external use only
Keep out of eyes, rinse with water to remove
Stop use and see a doctor if irritation develops and lasts.

Keep out of reach of children. Do not swallow. If swallowed, get medical help or contact a Poison Control Center right away.

Directions:

Apply daily after cleansing with Skin Effects Glycolic Cream cleanser

Apply to dry skin prior to make-up

Inactive Ingredients:

Water, Glycolic Acid, Glycerin, Cetyl Alcohol, Methyl Methyl acrylate/Glycol Dimethyacrylate Crosspolymer, Ammonium Hydroxide, Dimethicone, Potassium Ctyl Phosphate, Hydrogenated Palm Glycerides, methyl Glucose Sesquistearate, Butylene Glycol, Phenoxyethanol, Glyceryl Stearate, PEG 100 Stearate, Panthenol, tocopheryl Acetate, Bentonite, Xanthan Gum, Camellia Oleifera Leaf Extract, Disodium EDTA, Allantoin, Ethylhexylglycerin

PACKAGE LABEL

SKIN EFFECTS BY DR JEFFREY DOVER

Glycolic Day Cream SPF 30

Apply daily after cleansing withSkin Effects Glycolic Cream Cleanser

Apply to dry skin prior to makeup.

1 fl. oz. (30 ml)

Distributed by

Advanced health Care Distibutors, LLC

Concord, NH 03301

Questions or comments? Call toll free 1-866-428-7327

To find the Skin Effects regiment that is right for you go to www.skineffectsbydrdover.com

Skin Effects does not test on animals.

PACKAGE LABEL

SKIN EFFECTS BY DR. JEFFREY DOVER

Glycolic Day Cream SPF 30

Reduces the appearance of fine lines and wrinkles

Helps fight visible signs of aging.

1 fl. oz. (30 ml)

DESCRIPTION

Glycolic Acid: Alleviates and/or improves the appearance of aging skin including lines, blotches, blemishes, wrinkles, pigmented spots, atrophy, coarse rough, dry and yellowish skin, and other skin changes or skin damage caused by environmental factors such as sunlight, radiation, air pollution, wind, cold, dampness, heat chemicals and smoke.

WARNINGS

Avoid eye area. Discontinue use if signs of irritation develop. Keep out of reach of children. For external use only, do not swallow.

Glycolic Day Cream SPF 30

"Glycolic day cream spf 30 will hydrate, refresh and clarify your skin all day long while protecting your skin from the damaging rays of the sun. I believe in creating skin care products that deliver the results you want for smoother, younger looking skin."

Dr. Jeffrey Dover

This dynamic day cream will shield your skin from aging UVA and UVB rays while actively enhancing your complexion's appearance all day long. Daily use reduces the look of fine lines and wrinkles.

Reduces the appearance of wrinkles, fine lines and sun damage.

Hydrates to improve skins elasticity.

DOSAGE AND ADMINISTRATION

Directions: Apply daily after cleansing with Skin Effects Glycolic Cream Cleanser. Apply to dry skin prior to make up

Caring for your skin is a simple 3-step process :

1. Cleanse your skin

2. Treat signs of aging

3. Prevent sun damage by using Skin Effects moisturizer with SPF protection every day.

Distributed by Advanced Health Care Distributors, LLC

Concord NH 03301

Questions or Comments?

Call Toll Free 1-866-428-7327

To find the Skin Effects regimen that is right for you, go to www.skineffectsbydrdover.com

Skin Effects does not test on Animals.